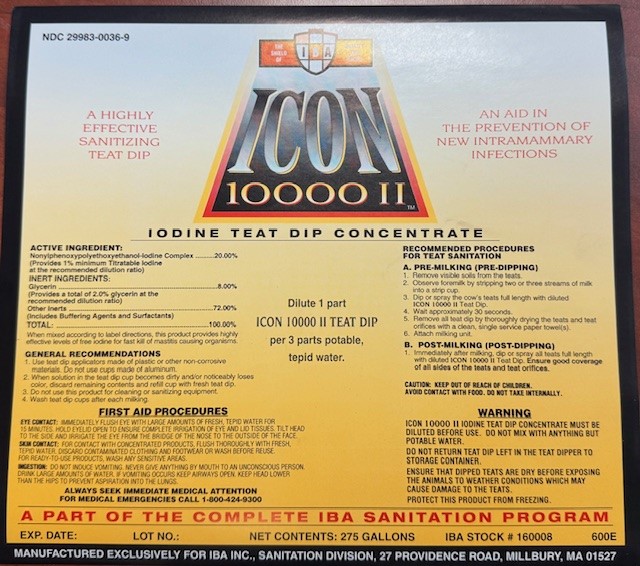 DRUG LABEL: ICON 10000 II
NDC: 29983-0036 | Form: SOLUTION, CONCENTRATE
Manufacturer: IBA
Category: animal | Type: OTC ANIMAL DRUG LABEL
Date: 20241231

ACTIVE INGREDIENTS: IODINE 40 g/1 L
INACTIVE INGREDIENTS: NONOXYNOL-12

ICON 10000 II IODINE TEAT DIP CONCENTRATE.
A HIGHLY EFFECTIVE SANITIZING TEAT DIP.
AN AID IN THE PREVENTION OF THE NEW INTRAMAMAMMARY INFECTIONS.

ACTIVE INGREDIENT

Nonylphenoxypolyethoxyethanol-Iodine Complex.....20.00%
(PROVIDES 1% minimum Titratable Iodine AT THE RECOMMENDED DILUTION RATIO)
INERT INGREDIENTS
Glycerin.......................8.00%
(Provides a total of 2.0% glycerin at the recommended dilution ratio)
Other inerts................72.00%
(Includes Buffering Agents and Surfactants)
TOTAL.................100%

When mixed according to label directions, this product provides highly effective levels of free iodine for fast kill of mastitis causing organisms.

INDICATIONS AND USAGE

Dilute to 1 Part ICON 10000 II TEAT DIP CONCENTRATE PER 3 PARTS POTABLE TEPID WATER

GENERAL RECOMMENDATIONS
1. Use teat dip applicators made of plastic or other non-corrosive materials. Do not use cups made of aluminum.
2. When solution in the teat dip cup becomes dirty and/or noticeably loses color, discard remaining contents and refill cup with fresh teat dip.
3. Do not use this product for cleaning or sanitizing equipment
4. Wash Teat Dip cups after each milking.

RECOMMENDED PROCEDURES FOR TEAT SANITATION
A. PRE-MILKING (PRE-DIPPING)
1. REMOVE VISIBLE SOILS FROM THE TEATS.
2. OBSERVE FOREMILK BY STRIPPING TWO OR THREE STREAMS OF MILK INTO A STRIP CUP.
3. DIP OR SPRAY THE COW'S TEATS FULL LENGTH WITH DILUTED ICON 10000 II TEAT DIP.
4 WAIT APPROXIMATELY 30 SECONDS.
5. REMOVE ALL TEAT DIP BY THOROUGHLY DRYING THE TEATS AND TEAT ORIFICES WITH A CLEAN, SINGLE SERVICE PAPER TOWEL(S).
6. ATTACH MILKING UNIT
B. POST-MILKING (POST DIPPING)
Immediately after milking dip all teats full length with DILUTED ICON 10000 II TEAT DIP Teat Dip Ensure good coverage of all sides of the teats and teat orifices.

WARNING

ICON 10000 II TEAT DIP CONCENTRATE MUST BE DILUTED BEFORE USE.
DO NOT MIX WITH ANYTHING BUT POTABLE WATER.
DO NOT RETURN TREAT DIP LEFT IN THE TEAT DIPPER TO STORAGE CONTAINER.
ENSURE THAT DIPPED TEATS ARE DRY BEFORE EXPOSING THE ANIMALS TO WEATHER CONDITIONS WHICH MAY CAUSE DAMAGE TO THE TEATS.
PROTECT THIS PRODUCT FROM FREEZING.

FIRST AID PROCEDURES

EYE CONTACT: IMMEDIATELY FLUSH EYE WITH LARGE AMOUNTS OF FRESH, TEPID WATER FOR 15 MINUTES. HOLD EYELID OPEN TO ENSURE COMPLETE IRRIGATION OF EYE AND LID TISSUES. TILT HEAD TO THE SIDE AND IRRIGATE THE EYE FROM THE BRIDGE OF THE NOSE TO THE OUTSIDE OF THE FACE.
SKIN CONTACT: WASH ANY SENSITIVE AREAS.
INGESTION: DO NOT INDUCE VOMITING. NEVER GIVE ANYTHING BY MOUTH TO AN UNCONSCIOUS PERSON. DRINK LARGE AMOUNTS OF WATER. IF VOMITING OCCURS KEEP AIRWAYS OPEN. KEEP HEAD LOWER THAN THE HIPS TO PREVENT ASPIRATION INTO THE LUNGS.

ALWAYS SEEK IMMEDIATE MEDICAL ATTENTION FOR MEDICAL EMERGENCIES CALL 1-800-424-9300